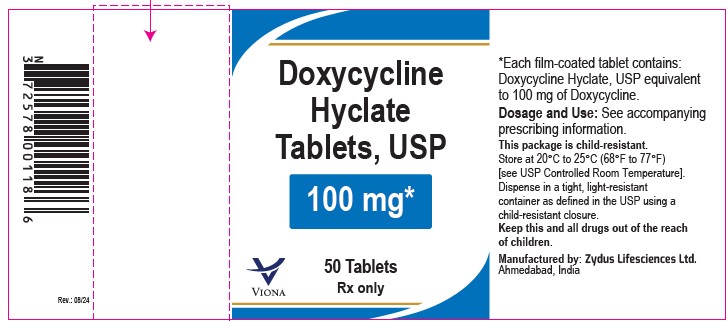 DRUG LABEL: Doxycycline hyclate
NDC: 70771-1104 | Form: TABLET
Manufacturer: Zydus Lifesciences Limited
Category: prescription | Type: HUMAN PRESCRIPTION DRUG LABEL
Date: 20240816

ACTIVE INGREDIENTS: DOXYCYCLINE HYCLATE 100 mg/1 1
INACTIVE INGREDIENTS: ANHYDROUS LACTOSE; CELLULOSE, MICROCRYSTALLINE; CROSCARMELLOSE SODIUM; FERRIC OXIDE RED; FERRIC OXIDE YELLOW; HYPROMELLOSES; MAGNESIUM STEARATE; POLYETHYLENE GLYCOL, UNSPECIFIED; SILICON DIOXIDE; STARCH, CORN; TITANIUM DIOXIDE

Doxycycline hyclate Tablets

PACKAGE LABEL.PRINCIPAL DISPLAY PANEL

NDC 70771-1104-7

Doxycycline Hyclate Tablets, 100 mg

Rx only

50 tablets